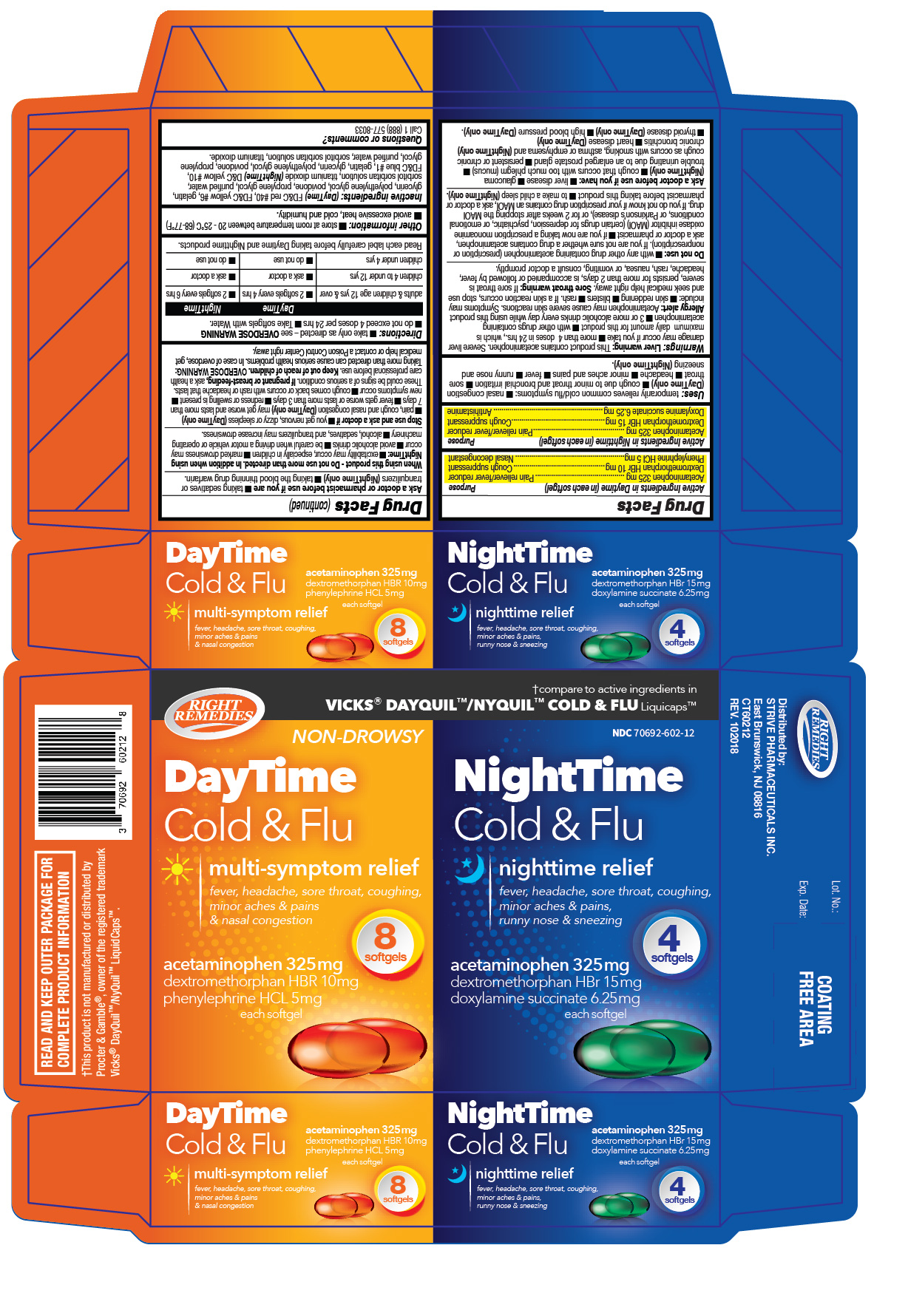 DRUG LABEL: DAYTIME NIGHTTIME Cold and Flu
NDC: 70692-602 | Form: KIT | Route: ORAL
Manufacturer: Strive Pharmaceuticals Inc.
Category: otc | Type: HUMAN OTC DRUG LABEL
Date: 20220412

ACTIVE INGREDIENTS: DEXTROMETHORPHAN HYDROBROMIDE 10 mg/1 1; ACETAMINOPHEN 325 mg/1 1; PHENYLEPHRINE HYDROCHLORIDE 5 mg/1 1; DOXYLAMINE SUCCINATE 6.25 mg/1 1; DEXTROMETHORPHAN HYDROBROMIDE 15 mg/1 1; ACETAMINOPHEN 325 mg/1 1
INACTIVE INGREDIENTS: SORBITOL; TITANIUM DIOXIDE; POLYETHYLENE GLYCOL 400; POVIDONE; FD&C YELLOW NO. 6; GELATIN; FD&C RED NO. 40; WATER; GLYCERIN; PROPYLENE GLYCOL; TITANIUM DIOXIDE; SORBITOL; POLYETHYLENE GLYCOL 400; D&C YELLOW NO. 10; FD&C BLUE NO. 1; GELATIN; WATER; GLYCERIN; POVIDONE; PROPYLENE GLYCOL

DAYTIME NIGHTTIME COLD and FLU

Active ingredients (in each Softgel) (Daytime) | Purpose
Acetaminophen 325mg | Pain Reliever/fever reducer
Dextromethorphan HBr 10mg | Cough suppressant
Phenylephrine HCl 5mg | Nasal Decongestant

Active ingredients (in each Softgel) (Nighttime) | Purpose
Acetaminophen 325mg | Pain Reliever/fever reducer
Dextromethorphan HBr 15mg | Cough suppressant
Docylamine Succinate 6.25mg | Antihistamine

PURPOSE

Daytime

Pain reliever/fever reducer, Cough suppresant and Nasal decongestant

Nighttime

Pain reliever/fever reducer, Cough suppressant and Antihistamine

INDICATIONS AND USAGE

* temporarily relieves common cold/flu symptoms:

- nasal congestion (Daytime only)
- cough due to minor throat and bronchial irritation
- sore throat
- headache
- minor aches and pains
- fever
- runny nose and sneezing (Nighttime only)

WARNINGS

Liver warning:
This product contains acetaminophen. Severe liver damage may occur if you take:
*more than 4 doses in 24 hrs, which is the maximum daily amount for this product
* with other drugs containing acetaminophen
*3 or more alcoholic drinks every day while using this product
Allergy alert:
Acetaminophen may cause severe skin reactions. Symptoms may include:
*skin reddening
*blisters
*rash
If a skin reaction occurs, stop use and seek medical help right away.

Sore throat warning:

if sore throat is severe, persists for more than 2 days, is accompanied or followed by fever, headache, rash, nausea, or vomiting, consult a doctor promptly.

Do not use
*with any other drug containing acetaminophen (prescription or nonprescription). If you are not sure whether a drug contains acetaminophen, ask a doctor or pharmacist.
* if you are now taking a prescription monoamine oxidase inhibitor (MAOI) (certain drugs for depression, psychiatric or emotional conditions, or Parkinson's disease), or for 2 weeks after stopping the MAOI drug. If you do not know if your prescription drug contains an MAOI, ask a doctor or pharmacist before taking this product.

*to make a child sleep (Nighttime only).

Ask a doctor before use if you have

* liver disease
* heart disease (Daytime only)
* high blood pressure (Daytime only)
* thyroid disease (Daytime only)
* trouble urinating due to an enlarged prostate gland
* glaucoma (Nighttime only)
* persistent or chronic cough such as occurs with smoking, asthma or emphysema and (Nighttime only) chronic bronchitis
* cough that occurs with too much phlegm (mucus)

Ask a doctor or a pharmacist before use if you are
* taking the blood thinning drug warfarin
* taking sedatives or tranquilizers (Nighttime only)
When using this product
Do not use more than directed. In addition when using Nighttime:
* excitability may occur, especially in children
* marked drowsiness may occur
* alcohol, sedatives, and tranquilizers may increase drowsiness
* be careful when driving a motor vehicle or operating machinery
* avoid alcoholic drinks

Stop use and ask a doctor if
* you get nervous, dizzy, or sleepless (Daytime only)
* pain, cough and nasal congestion (Daytime only) may get worse or lasts more than 7 days
* new symptoms occur
* fever gets worse or lasts more than 3 days
* redness or swelling is present
* cough comes back or occurs with rash or headache that lasts
These could be signs of a serious condition

If pregnant or breast-feeding,
ask a health care professional before use.
Keep out of reach of children

OVERDOSE WARNING:
Taking more than directed can cause serious health problems. In case of overdose, get medical help or contact a Poison Control Center right away.

Keep out of reach of children
OVERDOSE WARNING:

Taking more than directed can cause serious health problems. In case of overdose, get medical help or contact a Poison Control Center right away.

Directions
* take only as directed - see OVERDOSE WARNING

* do not exceed 4 doses per 24 hrs
* take softgels with water

Read each label carefully before taking Daytime and Nighttime product

 | Daytime | Nighttime
adulta & children age 12 years & over | 2 softgels every 4 hours | 2 softgels every 6 hours
children 4 to under 12 years | ask a doctor | ask a doctor
children under 4 years | do not use | do not use

Other information
* store at room temperature between 20 - 25°C (68 - 77°F)

*avoid excessive heat, cold and humidity

Inactive ingredients (Daytime)
FD&C red #40, FD&C yellow #6, gelatin, glycerin, polyethylene glycol, povidone, propylene glycol, purified water, sorbitol sorbitan solution, titanium dioxide.

Inactive ingredients (Nightime)
D&C yellow #10, FD&C blue #1, gelatin, glycerin, polyethylene glycol, povidone, propylene glycol, purified water, sorbitol sorbitan solution, titanium dioxide.